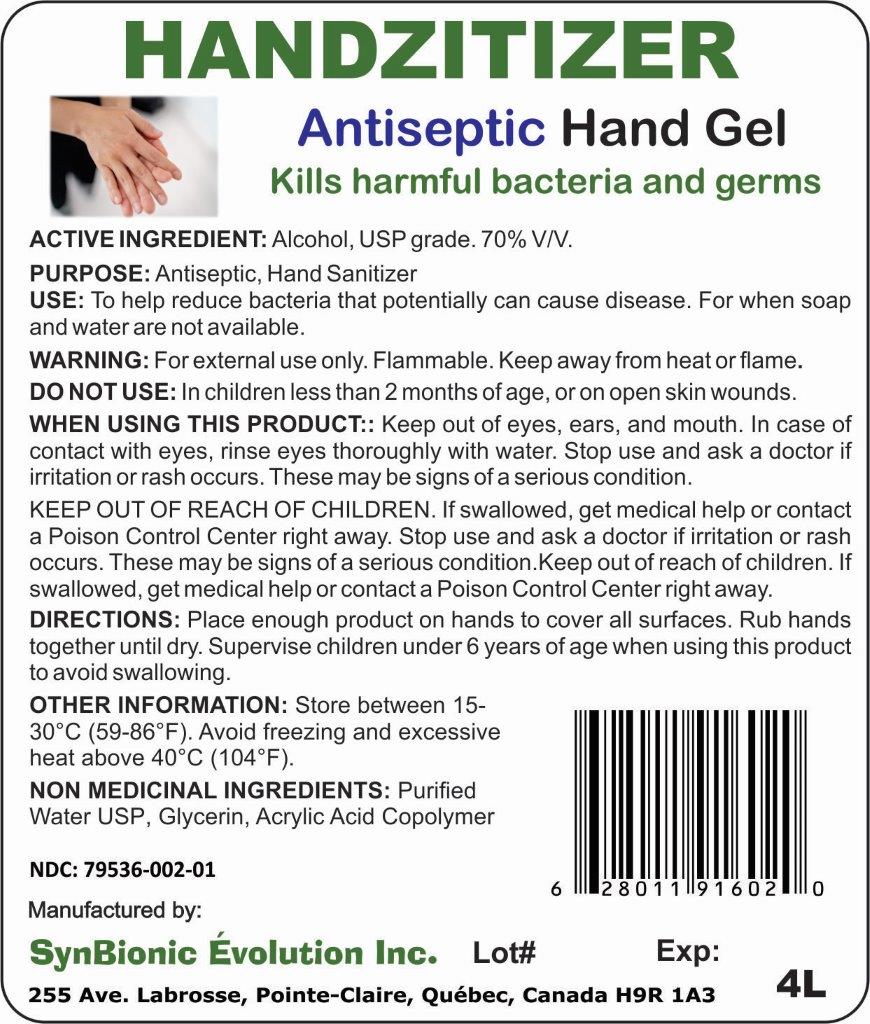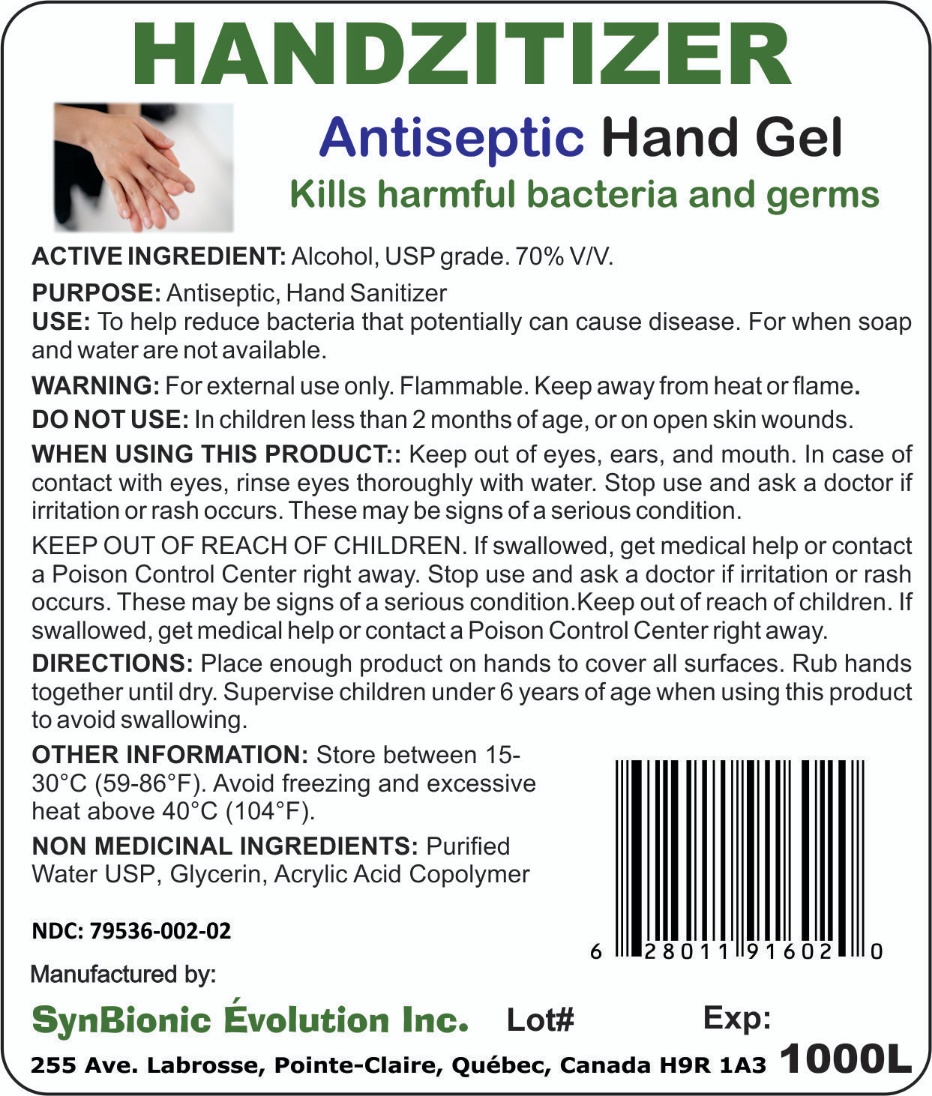 DRUG LABEL: Handzitizer
NDC: 79536-002 | Form: GEL
Manufacturer: SYNBIONIC EVOLUTION, INC.
Category: otc | Type: HUMAN OTC DRUG LABEL
Date: 20201109

ACTIVE INGREDIENTS: ALCOHOL 70 mL/100 mL
INACTIVE INGREDIENTS: CARBOMER 934; GLYCERIN; TROLAMINE; WATER

Handzitizer

Directions:

Place enough product on hands to cover all surfaces. Rub hands together until dry. Supervise children under 6 years of age when using this product to avoid swallowing.

Warning

For external use only. Flammable. Keep away from heat or open flame.

Non medicinal ingredients

Purified water USP, Glycerin, Acrylic Acid Copolymer

Use

To help reduce bacteria that potentially can cause disease. For when soap and water are not available.

KEEP OUT OF REACH OF CHILDREN

If swallowed, get medical help or contact a Poison Control Center right away. Stop use and ask a doctor if irritation or rash occurs. These may be signs of a serious condition.

Purpose

Antiseptic, Hand Sanitizer

Active Ingredient:

Alcohol, USP grade. 70% V/V